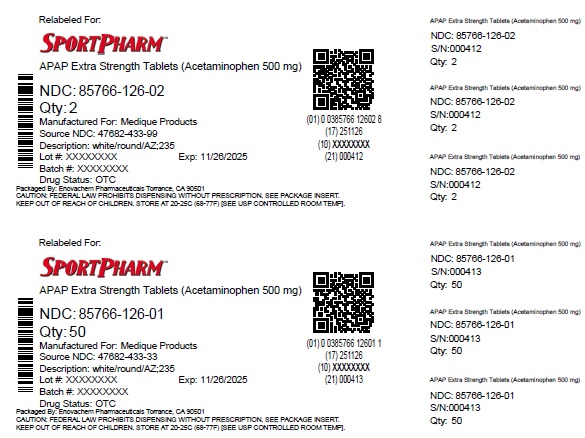 DRUG LABEL: Medique at Home APAP Extra Strength
NDC: 85766-126 | Form: TABLET, FILM COATED
Manufacturer: Sportpharm, Inc. dba Sportpharm
Category: otc | Type: HUMAN OTC DRUG LABEL
Date: 20251127

ACTIVE INGREDIENTS: ACETAMINOPHEN 500 mg/1 1
INACTIVE INGREDIENTS: POLYETHYLENE GLYCOL, UNSPECIFIED; HYPROMELLOSE, UNSPECIFIED; POVIDONE; STARCH, CORN; SODIUM STARCH GLYCOLATE TYPE A POTATO; STEARIC ACID; TITANIUM DIOXIDE

Medique @ Home APAP Extra Strength

Drug Facts

Active ingredient (in each tablet)

Acetaminophen 500 mg

PURPOSE

Puropse

Pain reliever/fever reducer

Uses

temporarily relieves minor aches and pains due to:

■ the common cold

■ headache

■ backache

■ minor pain of arthritis

■ toothache

■ muscular aches

■ premenstrual and menstrual cramps

temporarily reduces fever

Warnings

Liver warning:This product contains acetaminophen. Severe liver damage may occur if you take:

■ more than 4,000 mg of acetaminophen in 24 hours

■ with other drugs containing acetaminophen

■ 3 or more alcoholic drinks every day while using this product

Allergy alert:Acetaminophen may cause severe skin reactions. Symptoms may include:

■ skin reddening

■ blisters

■ rash

If a skin reaction occurs, stop use and seek medical help right away.

Do not use

■ with any other drug containing acetaminophen (prescription or nonprescription). If you are not sure whether a
drug contains acetaminophen, ask a doctor or pharmacist.

■ if you are allergic to acetaminophen or any of the inactive ingredients in this product

Ask a doctor before use if you haveliver disease

Ask a doctor or pharmacist before use ifyou are taking the blood thinning drug warfarin

Stop use and ask a doctor if

■ pain gets worse or lasts more than for more than 10 days

■ fever gets worse or lasts more than 3 days

■ new symptoms occur

■ redness or swelling is present

These could be signs of a serious condition.

PREGNANCY OR BREAST FEEDING

If pregnant or breast-feeding,ask a health professional before use.

Keep out of reach of children.

Overdose Warning:

In case of overdose, get medical help or contact a Poison Control Center right away (1-800-222-1222). Quick medical attention is critical for adults as well as for children even if you do not notice any signs or symptoms.

Directions

■ do not use more than directed (see overdose warning)

Adults and children 12 years and over■ take 2 tablets every 6 hours while symptoms last. ■ do not take more than 6 tablets in 24 hours, unless directed by a doctor ■ do not use for more than 10 days unless directed by a doctor

Children under 12 yearsAsk a doctor

Other information

■ store at room temperature 59º-86ºF (15º-30ºC)

■ TAMPER EVIDENTchild resistant packets

■ do not use any opened or torn packets

Inactive ingredients

corn starch, hypromellose, maltodextrin*, microcrystalline cellulose*, polyethylene glycol, povidone, pregelatinized starch*, sodium starch glycolate, stearic acid, titanium dioxide*

* may contain

Questions or comments?1-800-634-7680